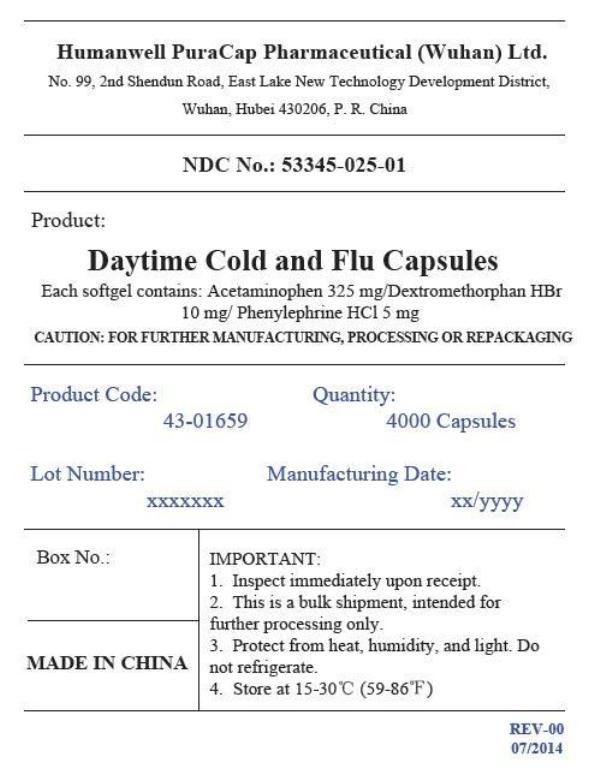 DRUG LABEL: DayTime Cold and Flu
NDC: 53345-025 | Form: CAPSULE, LIQUID FILLED
Manufacturer: Humanwell PuraCap Pharmaceutical (Wuhan), Ltd.
Category: otc | Type: HUMAN OTC DRUG LABEL
Date: 20241125

ACTIVE INGREDIENTS: ACETAMINOPHEN 325 mg/1 1; DEXTROMETHORPHAN HYDROBROMIDE 10 mg/1 1; PHENYLEPHRINE HYDROCHLORIDE 5 mg/1 1
INACTIVE INGREDIENTS: FD&C RED NO. 40; FD&C YELLOW NO. 6; GELATIN; GLYCERIN; POLYETHYLENE GLYCOL, UNSPECIFIED; POVIDONE; PROPYLENE GLYCOL; WATER; SORBITOL

DayTime Cold and Flu capsule, liquid filled

Active ingredients (in each capsule)

Acetaminophen 325 mg

Dextromethorphan HBr 10 mg

Phenylephrine HCl 5 mg

Purpose

Pain reliever/ fever reducer

Cough suppressant

Nasal decongestant

Uses

temporarily relieves common cold/flu symptoms:

- cough due to minor throat & bronchial irritation
- nasal congestion
- sore throat
- headache
- minor aches/pains
- fever

Warnings

Liver warning:This product contains acetaminophen. Severe liver damage may occur if you take:

- more than 4 doses in 24 hours, which is the maximum daily amount for this product
- with other drugs containing acetaminophen
- 3 or more alcoholic drinks daily while using this product

Sore throat warning:If sore throat is severe, persists more than 2 days, occurs with or is followed by fever, headache, rash, nausea, or vomiting, consult a doctor promptly.

Do not use

- with any other drug containing acetaminophen(prescription or nonprescription). If you are not sure whether a drug contains acetaminophen, ask a doctor or pharmacist.
- if you are now taking a prescription monoamine oxidase inhibitor (MAOI) (certain drugs for depression, psychiatric, or emotional conditions, or Parkinson's disease), or for 2 weeks after stopping the MAOI drug. If you do not know if your prescription drug contains an MAOI, ask a doctor or pharmacist before taking this product.

Ask a doctor before use if you have

- liver disease
- heart disease
- diabetes
- thyroid disease
- high blood pressure
- trouble urinating due to an enlarged prostate gland
- cough that occurs with too much phlegm (mucus)
- persistent or chronic cough as occurs with smoking, asthma, or emphysema

Ask a doctor or pharmacist before use if you are

taking the blood thinning drug warfarin

When using this product

- do not use more than directed

Stop use and ask a doctor if

- you get nervous, dizzy, or sleepless
- symptoms get worse or last more than 5 days (children) or 7 days (adults)
- fever gets worse or lasts more than 3 days
- redness or swelling is present
- new symptoms occur
- cough comes back, or occurs with rash or headache that lasts. These could be signs of a serious condition.

PREGNANCY OR BREAST FEEDING

If pregnant or breast-feeding,ask a health care professional before use.

Keep out of reach of children.

Overdose warning

Taking more than directed can cause serious health problems. In case of overdose, get medical help or contact a Poison Control Center right away. Quick medical attention is critical for adults and for children even if you do not notice any signs or symptoms.

Directions

- take only as directed - see Overdose warning
- do not exceed 4 doses per 24 hours

adults and children 12 years of age and older | take 2 softgels with water every 4 hours
children 4 to under 12 years of age | ask a doctor
children under 4 years of age | do not use

When using other Nighttime or Daytime products, carefully read each label to ensure correct dosing.

Other information

- store at room temperature 15°-30°C (59°-86°F)

Inactive ingredients

FD&C Red #40, FD&C Yellow #6, gelatin, glycerin, polyethylene glycol, povidone, propylene glycol, purified water, sorbitol special, white edible ink

Manufactured by:
Humanwell PuraCap Pharmaceutical (Wuhan) Ltd.
Wuhan, Hubei 430206,
China

PRINCIPAL DISPLAY PANEL - Shipping Label

DayTime Cold and Flu Capsules
Quantity : 4000 Capsules
NDC. No : 53345-025-01

IMPORTANT:

Inspect immediate upon receipt.
This is a bulk shipment intended for further processing only.
Protect from heat, humidity, and light. Do not refrigerate.
Store at 15-30°C (59-86°F)
CAUTION : "FOR FURTHER MANUFACTURING, PROCESSING OR REPACKAGING"